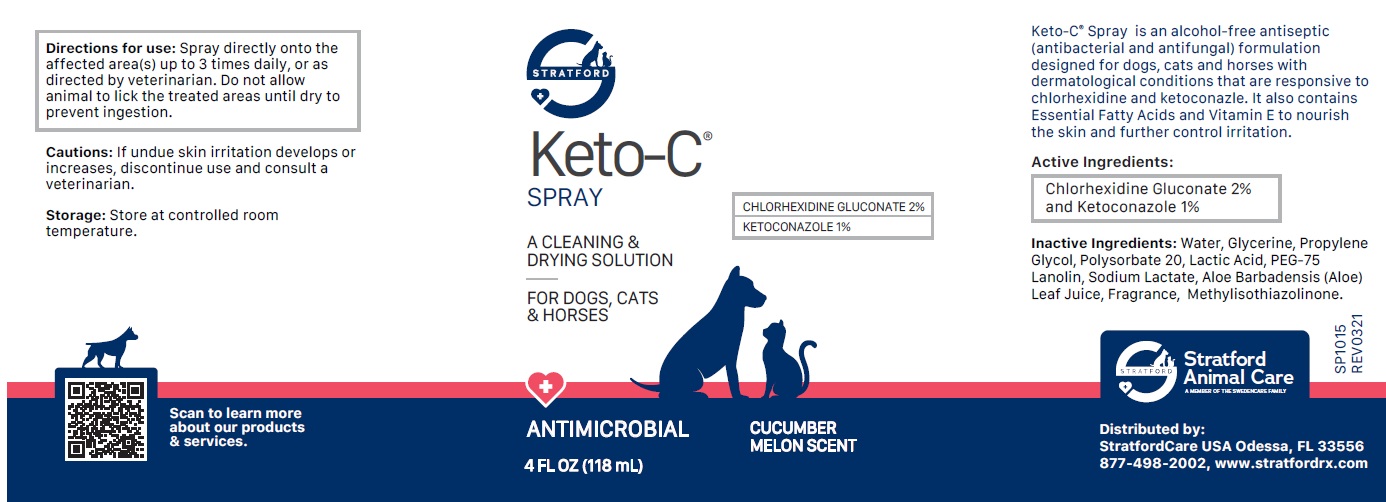 DRUG LABEL: Keto-C
NDC: 86069-103 | Form: SPRAY
Manufacturer: Stratford Care Usa, Inc.
Category: animal | Type: OTC ANIMAL DRUG LABEL
Date: 20221109

ACTIVE INGREDIENTS: CHLORHEXIDINE GLUCONATE 2 g/100 mL; KETOCONAZOLE 1 g/100 mL
INACTIVE INGREDIENTS: WATER; GLYCERIN; PROPYLENE GLYCOL; POLYSORBATE 20; LACTIC ACID, UNSPECIFIED FORM; PEG-75 LANOLIN; SODIUM LACTATE; ALOE VERA LEAF; METHYLISOTHIAZOLINONE

Keto-C® Spray

Active Ingredients:

Chlorhexidine Gluconate 2% and Ketoconazole 1%.

PURPOSE

antibacterial and antifungal

INDICATIONS AND USAGE

Keto-C® Spray is an alcohol-free antiseptic (antibacterial and antifungal) formulation designed for dogs, cats and horses with dermatological conditions that are responsive to chlorhexidine and ketoconazle. It also contains Essential Fatty Acids and Vitamin E to nourish the skin and further control irritation.

INACTIVE INGREDIENT

Inactive Ingredients: Water, Glycerin, Propylene Glycol, Polysorbate 20, Lactic Acid, PEG-75 Lanolin, Sodium Lactate, Aloe Barbadensis (Aloe) Leaf Juice, Fragrance, Methylisothiazolinone.

DOSAGE AND ADMINISTRATION

Directions for Use: Spray directly onto the affected area(s) up to 3 times daily, or as directed by veterinarian. Do not allow animal to lick the treated areas until dry to prevent ingestion.

PRECAUTIONS

Cautions: If undue skin irritation develops or increases, discontinue use and consult a veterinarian.

Storage: Store at controlled room temperature.

A CLEANING & DRYING SOLUTION

FOR DOGS, CATS & HORSES

ANTIMICROBIAL

CUCUMBER MELON SCENT

Stratford Animal Care
A MEMBER OF THE SWEDENCARE FAMILY

Distributed by:
StratfordCare USA Odessa, FL 33556
877-498-2002, www.stratfordrx.com